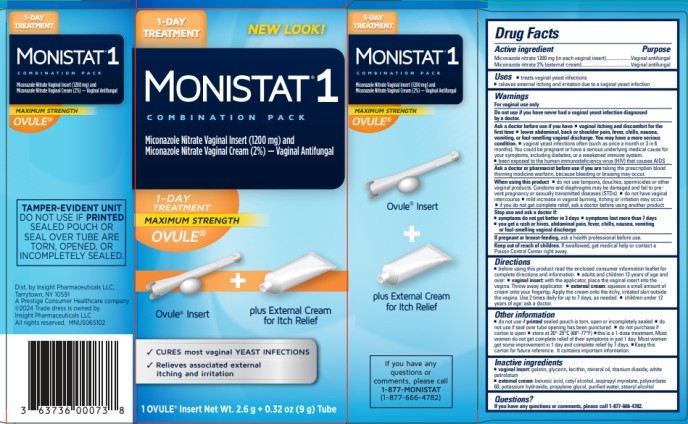 DRUG LABEL: Monistat 1 Combination Pack
NDC: 63736-013 | Form: KIT | Route: VAGINAL
Manufacturer: Insight Pharmaceuticals LLC
Category: otc | Type: HUMAN OTC DRUG LABEL
Date: 20250822

ACTIVE INGREDIENTS: Miconazole Nitrate 1200 mg/1 1; Miconazole Nitrate 20 mg/1 g
INACTIVE INGREDIENTS: Gelatin; Glycerin; Mineral Oil; Titanium Dioxide; Petrolatum; Benzoic Acid; Cetyl Alcohol; Isopropyl Myristate; Polysorbate 60; Potassium Hydroxide; Propylene Glycol; Water; Stearyl Alcohol

Monistat 1 COMBINATION PACK_Suppository-tube_63736-013-30

Drug Facts

Purpose

Miconazole nitrate 1200 mg (in vaginal insert) Vaginal antifungal

Miconazole nitrate 2% (external cream) Vaginal antifungal

Uses

- treats vaginal yeast infections
- relieves external itching and irritation due to a vaginal yeast infection

Warnings

For vaginal use only

Do not use

if you have never had a vaginal yeast infection diagnosed by a doctor.

Ask a doctor before use if you have

- vaginal itching and discomfort for the first time
- lower abdominal, back or shoulder pain, fever, chills, nausea, vomiting, or foul-smelling vaginal discharge. You may have a more serious condition.
- vaginal yeast infections often (such as once a month or 3 in 6 months). You could be pregnant or have a serious underlying medical cause for your symptoms, including diabetes or a weakened immune system.
- been exposed to the human immunodeficiency virus (HIV) that causes AIDS

Ask a doctor or pharmacist before use if you are

taking the prescription blood thinning medicine warfarin, because bleeding or bruising may occur

When using this product

- do not use tampons, douches, spermicides or other vaginal products. Condoms and diaphragms may be damaged and fail to prevent pregnancy or sexually transmitted diseases (STDs).
- do not have vaginal intercourse
- mild increase in vaginal burning, itching or irritation may occur
- if you do not get complete relief ask a doctor before using another product

Stop use and ask a doctor if

- symptoms do not get better in 3 days
- symptoms last more than 7 days
- you get a rash or hives, abdominal pain, fever, chills, nausea, vomiting, or foul-smelling vaginal discharge

If pregnant or breast-feeding,

ask a health professional before use.

Keep out of reach of children.

If swallowed, get medical help or contact a Poison Control Center right away.

Directions

- before using this product read the enclosed consumer information leaflet for complete directions and information
- adults and children 12 years of age and over:
  - vaginal insert: with the applicator, place the vaginal insert into the vagina. Throw applicator away.
  - external cream: squeeze a small amount of cream onto your fingertip. Apply the cream onto the itchy, irritated skin outside the vagina. Use 2 times daily for up to 7 days, as needed.
- children under 12 years of age: ask a doctor

Other information

- do not use if printed sealed pouch is torn, open or incompletely sealed
- do not use if seal over tube opening has been punctured
- do not purchase if carton is open
- store at 20°-25°C (68°-77°F)
- this is a 1-dose treatment. Most women do not get complete relief of their symptoms in just 1 day. Most women get some improvement in 1 day and complete relief by 7 days.
- Keep this carton for future reference. It contains important information.

Inactive ingredients

vaginal insert: gelatin, glycerin, lecithin, mineral oil, titanium dioxide, white petrolatum

external cream: benzoic acid, cetyl alcohol, isopropyl myristate, polysorbate 60, potassium hydroxide, propylene glycol, purified water, stearyl alcohol

Questions?

If you have any questions or comments, please call 1-877-666-4782.

PRINCIPAL DISPLAY PANEL

1-DAY
TREATMENT
NEW LOOK!

MONISTAT® 1
COMBINATION PACK

Miconazole Nitrate Vaginal Insert (1200 mg) and
Miconazole Nitrate Cream (2%) – Vaginal Antifungal
1-DAY
TREATMENT
MAXIMUM STRENGTH

1 OVULE® Insert Net Wt. 2.6 g +0.32oz (9g) Tube